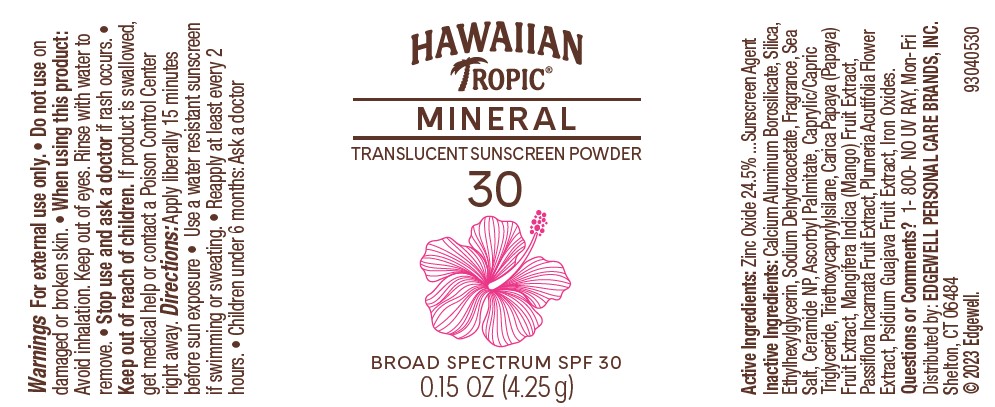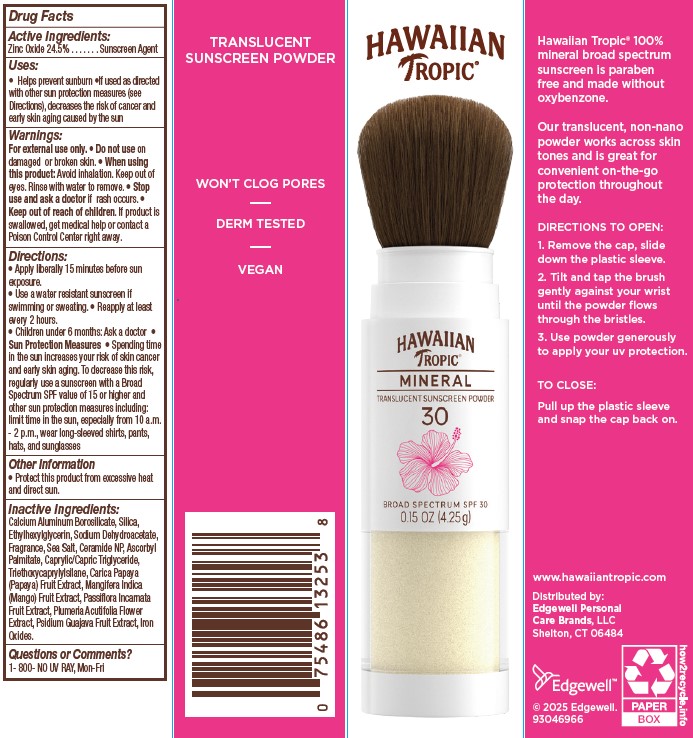 DRUG LABEL: Hawaiian Tropic Mineral Translucent Sunscreen Powder SPF 30
NDC: 63354-820 | Form: POWDER
Manufacturer: Edgewell Personal Care Brands LLC
Category: otc | Type: HUMAN OTC DRUG LABEL
Date: 20250928

ACTIVE INGREDIENTS: ZINC OXIDE 24.5 g/100 g
INACTIVE INGREDIENTS: MEDIUM-CHAIN TRIGLYCERIDES; ASCORBYL PALMITATE; FERRIC OXIDE YELLOW; ETHYLHEXYLGLYCERIN; CERAMIDE NP; FERROSOFERRIC OXIDE; MANGO; PLUMERIA RUBRA FLOWER; CALCIUM ALUMINUM BOROSILICATE; TRIETHOXYCAPRYLYLSILANE; GUAVA; SILICON DIOXIDE; SODIUM DEHYDROACETATE; FERRIC OXIDE RED; SEA SALT; PAPAYA; PASSIFLORA INCARNATA FRUIT

Active Ingredients:

Zinc Oxide 24.5%

Purpose

Sunscreen Agent

Uses:

• Helps prevent sunburn •If used as directed with other sun protection measures (see Directions), decreases the risk of cancer and
early skin aging caused by the sun

Warnings:

For external use only.

Do not use

on damaged or broken skin.

When using this product:

Avoid inhalation. Keep out of eyes. Rinse with water to remove.

Stop use and ask a doctor

if rash occurs.

Keep out of reach of children.

If product is swallowed, get medical help or contact a Poison Control Center right away.

Directions:

• Apply liberally 15 minutes before sun exposure. • Use a water resistant sunscreen if swimming or sweating. • Reapply at least every 2 hours. • Children under 6 months: Ask a doctor • Sun Protection Measures • Spending time in the sun increases your risk of skin cancer and early skin aging. To decrease this risk, regularly use a sunscreen with a Broad Spectrum SPF value of 15 or higher and other sun protection measures including: limit time in the sun, especially from 10 a.m. - 2 p.m., wear long-sleeved shirts, pants,
hats, and sunglasses

Inactive Ingredients:

Calcium Aluminum Borosilicate, Silica, Ethylhexylglycerin, Sodium Dehydroacetate, Fragrance, Sea Salt, Ceramide NP, Ascorbyl
Palmitate, Caprylic/Capric Triglyceride, Triethoxycaprylylsilane, Carica Papaya (Papaya) Fruit Extract, Mangifera Indica (Mango) Fruit Extract, Passiflora Incarnata Fruit Extract, Plumeria Acutifolia Flower Extract, Psidium Guajava Fruit Extract, Iron Oxides.

Other Information

Protect this product from excessive heat and direct sun.

Questions or Comments?

1- 800- NO UV RAY, Mon-Fri

Principal Display Panel

HAWAIIAN

Tropic (R)

MINERAL

TRANSLUCENT SUNSCREEN POWDER

30

BROAD SPECTRUM SPF 30

0.15 OZ. (4.25 g)

Carton

TRANSLUCENT

SUNSCREEN POWDER

WON'T CLOG PORES

DERM TESTED

VEGAN

HAWAIIAN

Tropic (R)

MINERAL

TRANSLUCENT SUNSCREEN POWDER

30

BROAD SPECTRUM SPF 30

0.15 OZ. (4.25 g)